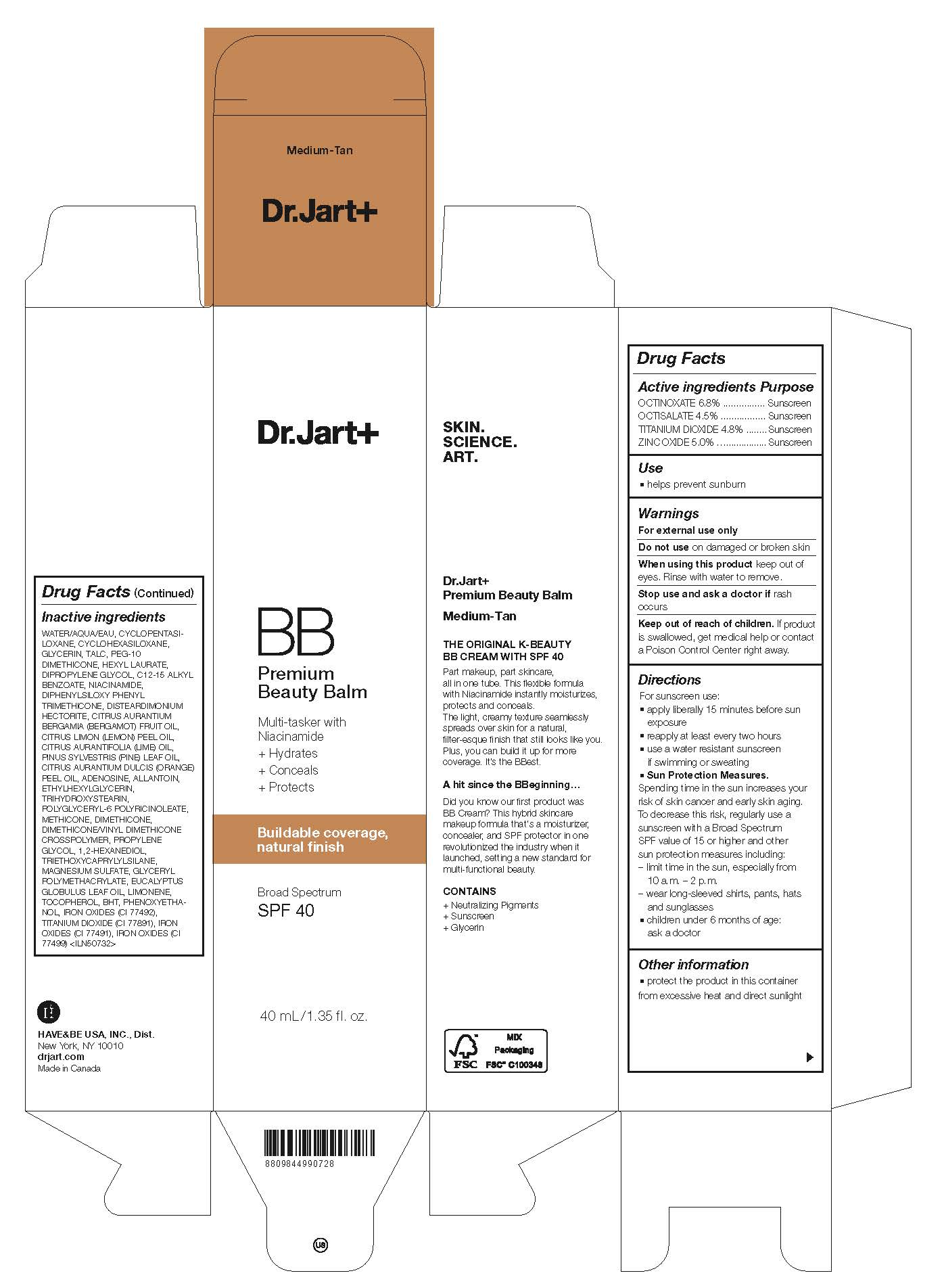 DRUG LABEL: Dr.Jart Premium Beauty Balm Medium-Tan
NDC: 49404-303 | Form: CREAM
Manufacturer: Have & Be Co., Ltd.
Category: otc | Type: HUMAN OTC DRUG LABEL
Date: 20250206

ACTIVE INGREDIENTS: TITANIUM DIOXIDE 48 mg/1 mL; ZINC OXIDE 50 mg/1 mL; OCTINOXATE 68 mg/1 mL; OCTISALATE 45 mg/1 mL
INACTIVE INGREDIENTS: CYCLOMETHICONE 5; CYCLOMETHICONE 6; GLYCERIN; PEG-10 DIMETHICONE (600 CST); WATER; TALC; ALKYL (C12-15) BENZOATE; HEXYL LAURATE; DIPHENYLSILOXY PHENYL TRIMETHICONE; NIACINAMIDE; DIPROPYLENE GLYCOL; DISTEARDIMONIUM HECTORITE; MAGNESIUM SULFATE, UNSPECIFIED FORM; DIMETHICONE/VINYL DIMETHICONE CROSSPOLYMER (HARD PARTICLE); DIMETHICONE; FERRIC OXIDE YELLOW; TRIETHOXYCAPRYLYLSILANE; PHENOXYETHANOL; FERRIC OXIDE RED; TOCOPHEROL; ALLANTOIN; 1,2-HEXANEDIOL; PROPYLENE GLYCOL; POLYSORBATE 80; PLATINUM; PALMITOYL TRIPEPTIDE-1; METHICONE (20 CST); FERROSOFERRIC OXIDE; POLYGLYCERYL-6 POLYRICINOLEATE; TRIHYDROXYSTEARIN; ETHYLHEXYLGLYCERIN; ADENOSINE; ORANGE OIL, COLD PRESSED; LIME OIL, COLD PRESSED; PINE NEEDLE OIL (PINUS SYLVESTRIS); BUTYLATED HYDROXYTOLUENE; EUCALYPTUS OIL; BERGAMOT OIL; LEMON OIL, COLD PRESSED

DR.JART PREMIUM BEAUTY BALM MEDIUM-TAN

ACTIVE INGREDIENT

OCTINOXATE 6.8%
OCTISALATE 4.5%
TITANIUM DIOXIDE 4.8%
ZINC OXIDE 5.0%

PURPOSE

Sunscreen

INDICATIONS AND USAGE

Helps prevent sunburn

DOSAGE AND ADMINISTRATION

For sunscreen use:
■ apply liberally 15 minutes before sun exposure
■ reapply at least every two hours
■ use a water resistant sunscreen if swimming or sweating
■ Sun Protection Measures.
Spending time in the sun increases your risk of skin cancer and early skin aging. To decrease this risk, regularly use a sunscreen with a Broad Spectrum SPF value of 15 or higher and other sun protection measures including:
– limit time in the sun, especially from 10 a.m. – 2 p.m.
– wear long-sleeved shirts, pants, hats and sunglasses
■ children under 6 months of age: ask a doctor

WARNINGS

For external use only.
Do not use on damaged or broken skin.
When using this product, keep out of eyes. Rinse with water to remove.
Stop using and ask a doctor if rash occurs.

KEEP OUT OF REACH OF CHILDREN

Keep out of reach of the children. If product is swallowed, get medical help or contact a poison control center right away.

INACTIVE INGREDIENT

WATER, CYCLOPENTASILOXANE, CYCLOHEXASILOXANE, GLYCERIN, TALC, PEG-10 DIMETHICONE, IRON OXIDES(CI 77492), C12-15 ALKYL BENZOATE, HEXYL LAURATE, DIPHENYLSILOXY PHENYL TRIMETHICONE, NIACINAMIDE, DIPROPYLENE GLYCOL, DISTEARDIMONIUM HECTORITE, TITANIUM DIOXIDE(CI 77891), MAGNESIUM SULFATE, DIMETHICONE/VINYL DIMETHICONE CROSSPOLYMER, DIMETHICONE, IRON OXIDES(CI 77491), TRIETHOXYCAPRYLYLSILANE, PHENOXYETHANOL, IRON OXIDES(CI 77499), METHICONE, POLYGLYCERYL-6 POLYRICINOLEATE, TRIHYDROXYSTEARIN, ETHYLHEXYLGLYCERIN, CITRUS AURANTIUM DULCIS (ORANGE) PEEL OIL, ADENOSINE, CITRUS AURANTIFOLIA (LIME) OIL, PINUS SYLVESTRIS LEAF OIL, BHT, EUCALYPTUS GLOBULUS LEAF OIL, CITRUS AURANTIUM BERGAMIA (BERGAMOT) FRUIT OIL, CITRUS LIMON (LEMON) PEEL OIL, TOCOPHEROL, ALLANTOIN, GLYCERYL POLYMETHACRYLATE, PROPYLENE GLYCOL, 1,2-HEXANEDIOL, POLYSORBATE 80, PLATINUM POWDER, PALMITOYL TRIPEPTIDE-1

OTHER SAFETY INFORMATION

Protect the product in this container from excessive heat and direct sunlight